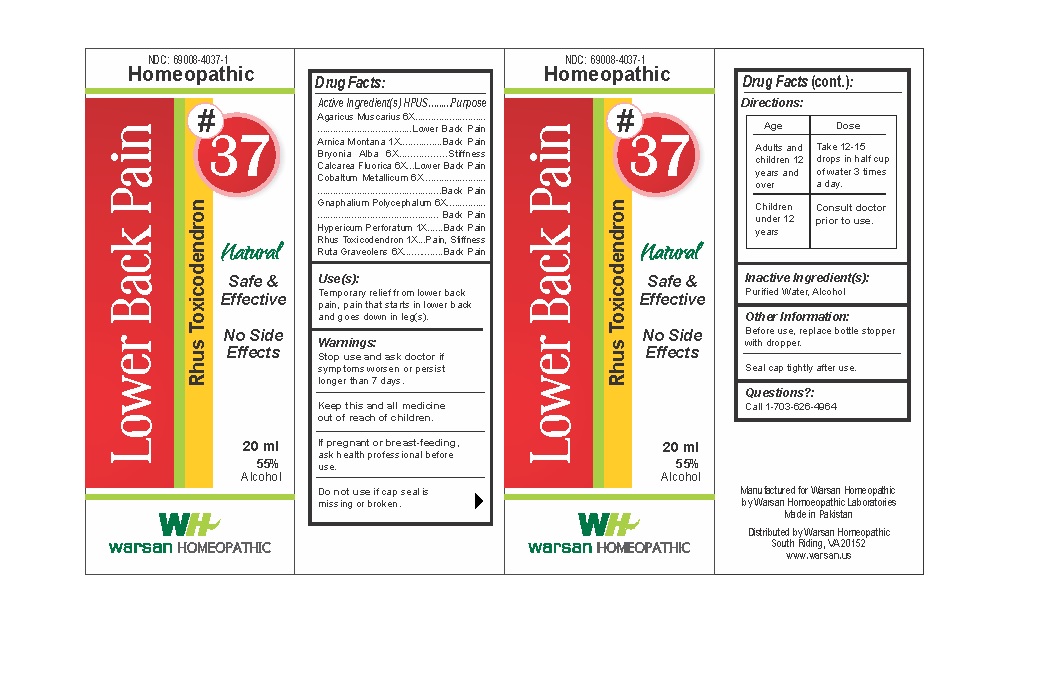 DRUG LABEL: Combination Remedy 37 - Low Back Pain
NDC: 69008-4037 | Form: SOLUTION/ DROPS
Manufacturer: Warsan Homoeopathic Laboratories
Category: homeopathic | Type: HUMAN OTC DRUG LABEL
Date: 20171225

ACTIVE INGREDIENTS: BRYONIA ALBA ROOT 6 [hp_X]/1 mL; CALCIUM FLUORIDE 6 [hp_X]/1 mL; AMANITA MUSCARIA FRUITING BODY 6 [hp_X]/1 mL; PSEUDOGNAPHALIUM OBTUSIFOLIUM 6 [hp_X]/1 mL; HYPERICUM PERFORATUM 1 [hp_X]/1 mL; ARNICA MONTANA 1 [hp_X]/1 mL; COBALT 6 [hp_X]/1 mL; TOXICODENDRON PUBESCENS LEAF 1 [hp_X]/1 mL; RUTA GRAVEOLENS FLOWERING TOP 6 [hp_X]/1 mL
INACTIVE INGREDIENTS: ALCOHOL; WATER

Stop use and ask doctor if symptoms worsen or persist longer than 7 days.

If pregnant or breast-feeding, ask health professional before use.

Do not use if tamper evident seal is missing or broken.

Keep out of reach of children.

ACTIVE INGREDIENT

Agaricus Muscarius 6X

Arnica Montana 1X

Bryonia Alba 6X

Calcarea Fluorica 6X

Cobaltum Metallicum 6X

Gnaphalium Polycephalum 6X

Hypericum Perforatum 1X

Rhus Toxicodendron 1X

Ruta Graveolens 6X

PURPOSE

Temporary relief from lower back pain, pain that starts in lower back and goes down in leg(s)..

INACTIVE INGREDIENT

Purified Water

Alcohol

DOSAGE AND ADMINISTRATION

Adults 18 years and older: Take 10-15 drops in half cup of water 3 times a day.

INDICATIONS AND USAGE

Temporary relief from lower back pain, pain that starts in lower back and goes down in leg(s).